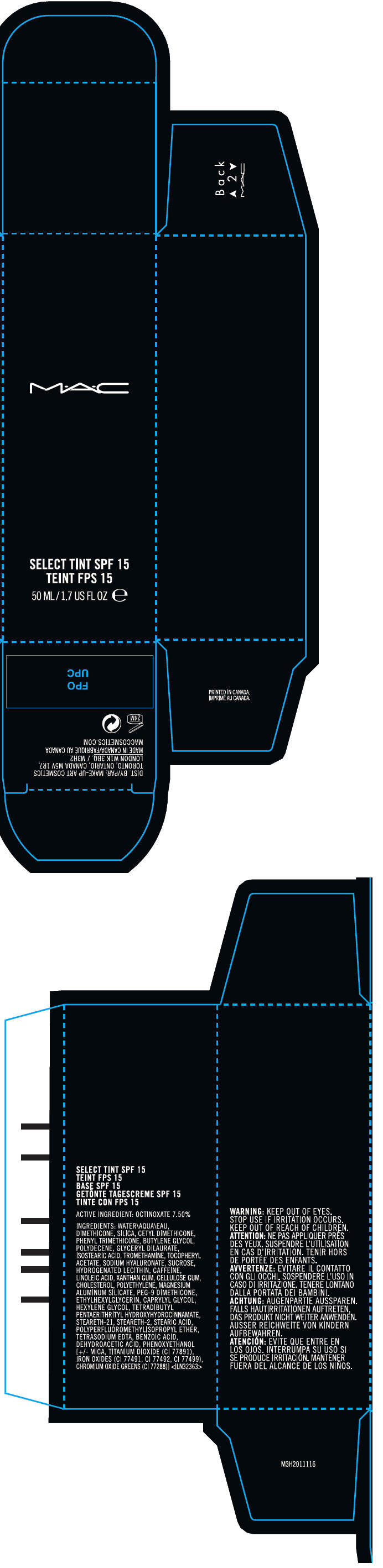 DRUG LABEL: MAC
NDC: 40046-0055 | Form: LIQUID
Manufacturer: MAKEUP ART COSMETICS
Category: otc | Type: HUMAN OTC DRUG LABEL
Date: 20120502

ACTIVE INGREDIENTS: OCTINOXATE 7.5 mL/100 mL
INACTIVE INGREDIENTS: WATER; DIMETHICONE; SILICON DIOXIDE; PHENYL TRIMETHICONE; BUTYLENE GLYCOL; GLYCERYL DILAURATE; ISOSTEARIC ACID; TROMETHAMINE; .ALPHA.-TOCOPHEROL ACETATE; HYALURONATE SODIUM; SUCROSE; CAFFEINE; LINOLEIC ACID; XANTHAN GUM; CARBOXYMETHYLCELLULOSE SODIUM; CHOLESTEROL; HIGH DENSITY POLYETHYLENE; MAGNESIUM ALUMINUM SILICATE; ETHYLHEXYLGLYCERIN; CAPRYLYL GLYCOL; HEXYLENE GLYCOL; STEARETH-21; STEARETH-2; STEARIC ACID; EDETATE SODIUM; BENZOIC ACID; DEHYDROACETIC ACID; PHENOXYETHANOL; MICA; TITANIUM DIOXIDE; FERRIC OXIDE RED; FERRIC OXIDE YELLOW; FERROSOFERRIC OXIDE; CHROMIC OXIDE

M•A•C
SELECT TINT SPF 15

ACTIVE INGREDIENT

OCTINOXATE 7.50%

INGREDIENTS

WATER\AQUA\EAU, DIMETHICONE, SILICA, CETYL DIMETHICONE, PHENYL TRIMETHICONE, BUTYLENE GLYCOL, POLYDECENE, GLYCERYL DILAURATE, ISOSTEARIC ACID, TROMETHAMINE, TOCOPHERYL ACETATE, SODIUM HYALURONATE, SUCROSE, HYDROGENATED LECITHIN, CAFFEINE, LINOLEIC ACID, XANTHAN GUM, CELLULOSE GUM, CHOLESTEROL, POLYETHYLENE, MAGNESIUM ALUMINUM SILICATE, PEG-9 DIMETHICONE, ETHYLHEXYLGLYCERIN, CAPRYLYL GLYCOL, HEXYLENE GLYCOL, TETRADIBUTYL PENTAERITHRITYL HYDROXYHYDROCINNAMATE, STEARETH-21, STEARETH-2, STEARIC ACID, POLYPERFLUOROMETHYLISOPROPYL ETHER, TETRASODIUM EDTA, BENZOIC ACID, DEHYDROACETIC ACID, PHENOXYETHANOL [+/- MICA, TITANIUM DIOXIDE (CI 77891), IRON OXIDES (CI 77491, CI 77492, CI 77499), CHROMIUM OXIDE GREENS (CI 77288)] <ILN32363>

WARNING

WHEN USING

KEEP OUT OF EYES.

STOP USE IF IRRITATION OCCURS.

KEEP OUT OF REACH OF CHILDREN.

DIST. BY/PAR: MAKE-UP ART COSMETICS
TORONTO, ONTARIO, CANADA M5V 1R7,
LONDON W1K 3BQ. / M3H2

PRINCIPAL DISPLAY PANEL - 50 ML Bottle Carton

M•A•C

SELECT TINT SPF 15

50 ML/1.7 US FL OZ e